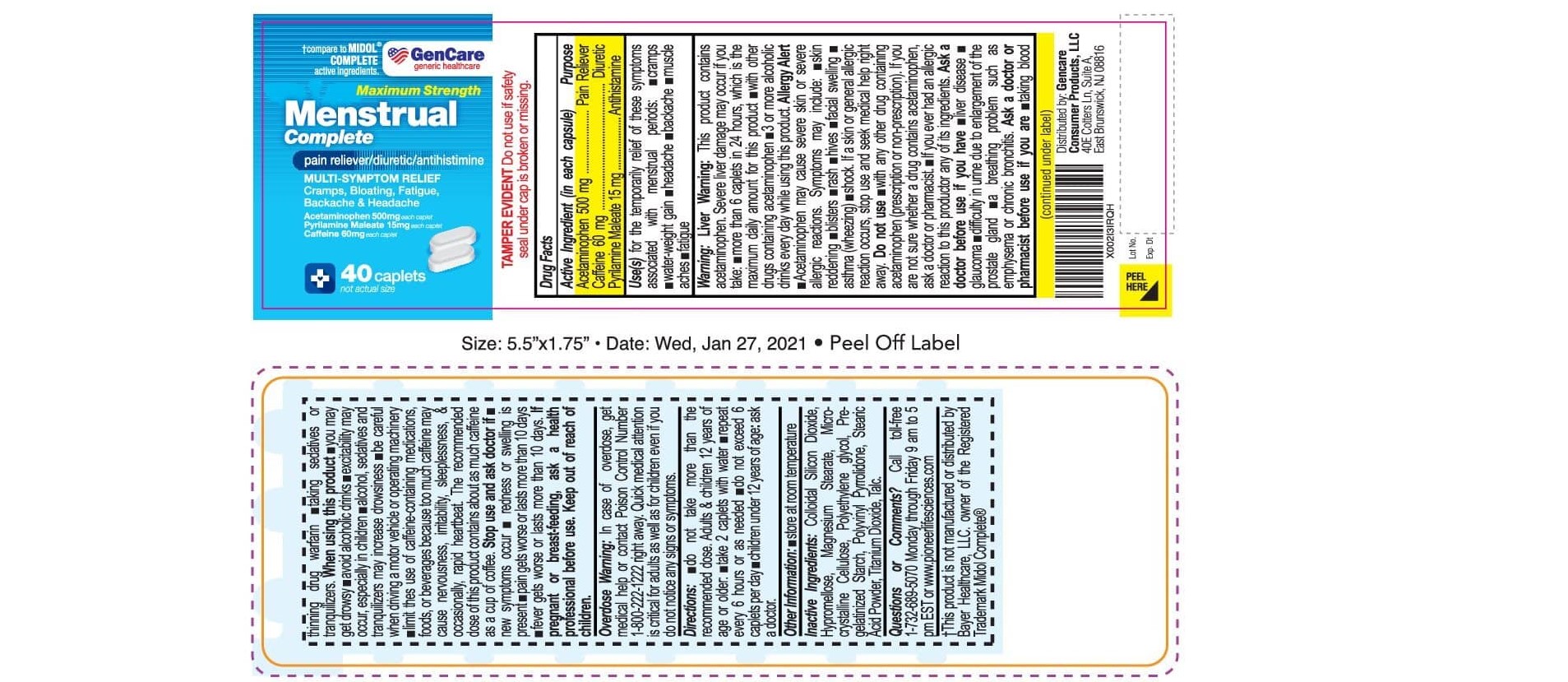 DRUG LABEL: Menstrual Complete
NDC: 72090-026 | Form: TABLET
Manufacturer: Pioneer Life Sciences, LLC
Category: otc | Type: HUMAN OTC DRUG LABEL
Date: 20251226

ACTIVE INGREDIENTS: CAFFEINE 60 mg/1 1; PYRILAMINE MALEATE 15 mg/1 1; ACETAMINOPHEN 500 mg/1 1
INACTIVE INGREDIENTS: SILICON DIOXIDE; HYPROMELLOSES; MAGNESIUM STEARATE; MICROCRYSTALLINE CELLULOSE; POLYETHYLENE GLYCOL, UNSPECIFIED; STARCH, CORN; POVIDONE; STEARIC ACID; TITANIUM DIOXIDE; TALC

Active Ingredient

Acetaminophen 500 mg
Caffeine 60 mg
Pyrilamine maleate 15 mg

Purpose

Pain reliever,Diuretic, Antihistamine

Uses:

for the temporary relief of these symptoms associated with menstrual periods:

- cramps
- water-weight gain
- headache
- backache
- muscle aches
- fatigue

Warnings:

Liver warning:

This product contains acetaminophen. Severe liver damage may occur if you take

- more than 6 caplets in 24 hours, which is the maximum daily amount for this product
- with other drugs containing acetaminophen
- 3 or more alcoholic drinks every day while using this product

Allergy alert:

- Acetaminophen may cause sever skin or sever allergy reactions. Symptoms may include:
- skin reddening
- blister
- rash
- hives
- facial swelling
- asthma (wheezing)
- shock

if a skin or general allergic reaction ocurs, stop use and seek medical help right away.

Do not use:

- with any other drug containing acetaminophen (prescription or nonprescription). If you are not sure whether a drug contains acetaminophen

ask a doctor or pharmacist

- if you have ever had an allergic reaction to this product or any of its ingredients

Ask Doctor:

Ask a doctor before use if you have -

- liver disease
- glaucoma
- difficulty in urine due to enlargement of the prostate gland
- a breathing problem such as emphysema or chronic bronchitis

ASK DOCTOR/PHARMACIST:

Ask a doctor or pharmacist before use if you are

- taking the blood thinning drug warfarin
- taking sedatives or tranquilizers

When using this Product

- you may get drowsy
- avoid alcoholic drinks
- excitability may occur, especially in children
- alcohol, sedatives, and tranquilizers may increase drowsiness
- be careful when driving a motor vehicle or operating machinery
- limit the use of caffeine-containing medications, foods, or beverages because too much caffeine may cause nervousness, irritability, sleeplessness, and, occasionally, rapid heartbeat. The recommended dose of this product contains about as much caffeine as a cup of coffee.

Stope use and Ask Doctor if

- new symptoms occur
- redness or swelling is present
- pain gets worse or lasts more than 10 days
- fever gets worse or lasts more than 3 days

PREGNANCY

If pregnant or breast-feeding, ask a health professional before use.

KEEP OUT OF REACH OF CHILDREN

Overdose Warning: In case of overdose, get medical help or contact a Poison Control Center (1-800-222-1222) right away. Quick medical attention is critical for adults as well as for children even if you do not notice any signs or symptoms.

DIRECTIONS

- do not take more than the recommended dose. adults and children 12 years of age or older
- take 2 caplets with water
- repeat every 6 hours, as needed
- do not exceed 6 caplets per day
- children under 12 years: ask a doctor

OTHER INFORMATION

store at room temperature

INACTIVE INGREDIENTS

Colliodal Silicon Dioxide, Hypromellose, Magnesium Stearate, Microcrystalline Cellulose, Polyethylene Glycol, Pregelatinized Starch, Polyvinyl Pyrrolidone, Stearaic Acid Powder, Titanium Dioxide, Talc

QUESTIONS OR COMMENTS?

Call 1-732-698-5070 Monday through Friday 9AM–5PM EST or www.pioneerlifesciences.com